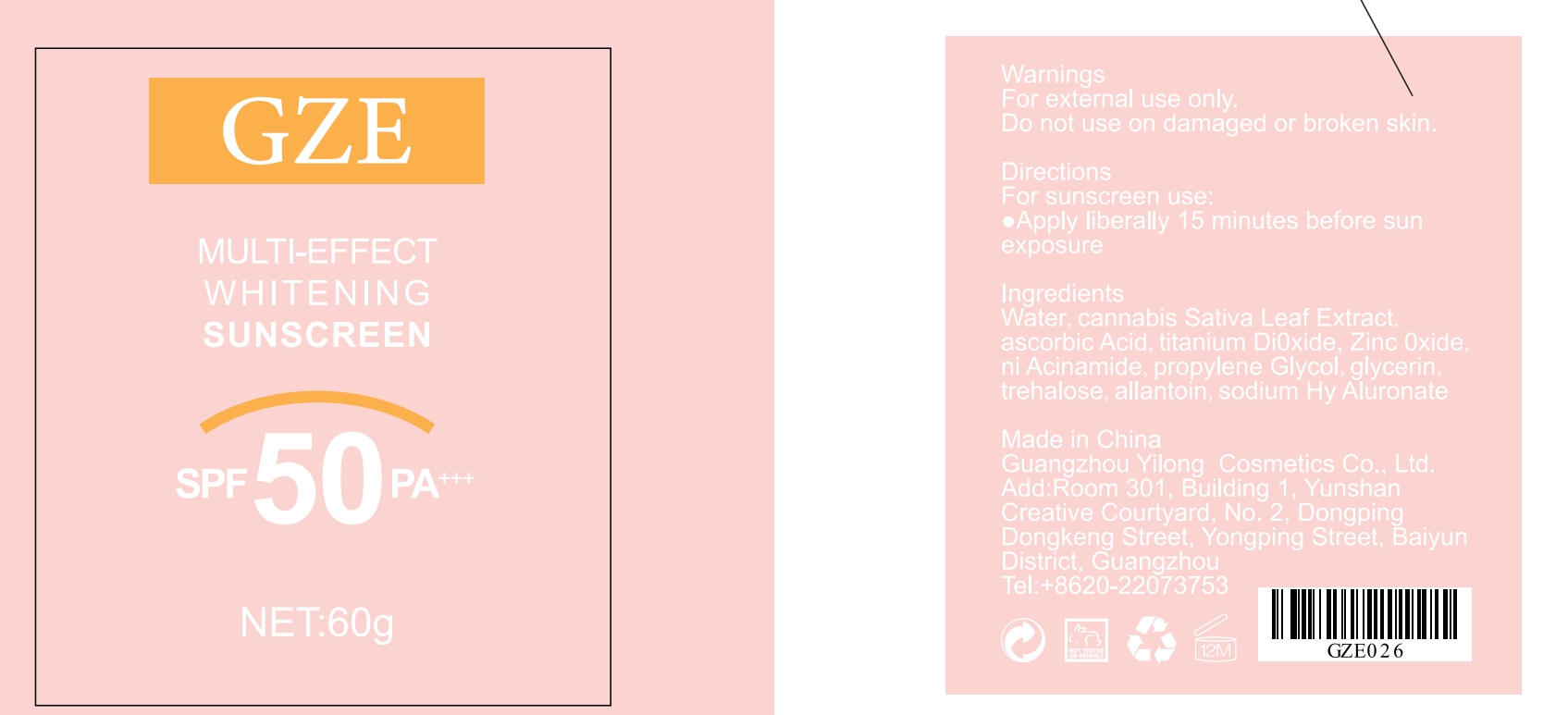 DRUG LABEL: GZE MULTI-EFFECT WHITENING SUNSCREEN
NDC: 74458-026 | Form: CREAM
Manufacturer: Guangzhou Yilong Cosmetics Co., Ltd
Category: otc | Type: HUMAN OTC DRUG LABEL
Date: 20241014

ACTIVE INGREDIENTS: TITANIUM DIOXIDE 10 g/100 g; ZINC OXIDE 10 g/100 g
INACTIVE INGREDIENTS: HYALURONATE SODIUM; CANNABIS SATIVA LEAF; NIACINAMIDE; GLYCERIN; ASCORBIC ACID; ALLANTOIN; WATER; TREHALOSE; PROPYLENE GLYCOL

GZE MULTI-EFFECT WHITENING SUNSCREEN

ACTIVE INGREDIENT

Titanium Dioxide

Zinc Oxide

Niacinamide

INACTIVE INGREDIENT

Aqua

Cannabis Sativa Leaf Extract

Ascorbic Acid

Propylene Glycol

Glycerin

Trehalose

Allantoin

Sodium Hyaluronate

PURPOSE

Whiten and protect against the sun

INDICATIONS AND USAGE

Apply liberally 15 minutes before sun exposure.

Stop use and ask a doctor if rash occurs.

WARNINGS

For external use only.

Do not use on damaged or broken skin.

When using this product keep out of eyes. Rinse with water to remove.

Keep out of reach of children. If swallowed, get medical help or contact a Poison Control Center right away.

DOSAGE AND ADMINISTRATION

Apply liberally 15 minutes before sun exposure.

Stop use and ask a doctor if rash occurs.